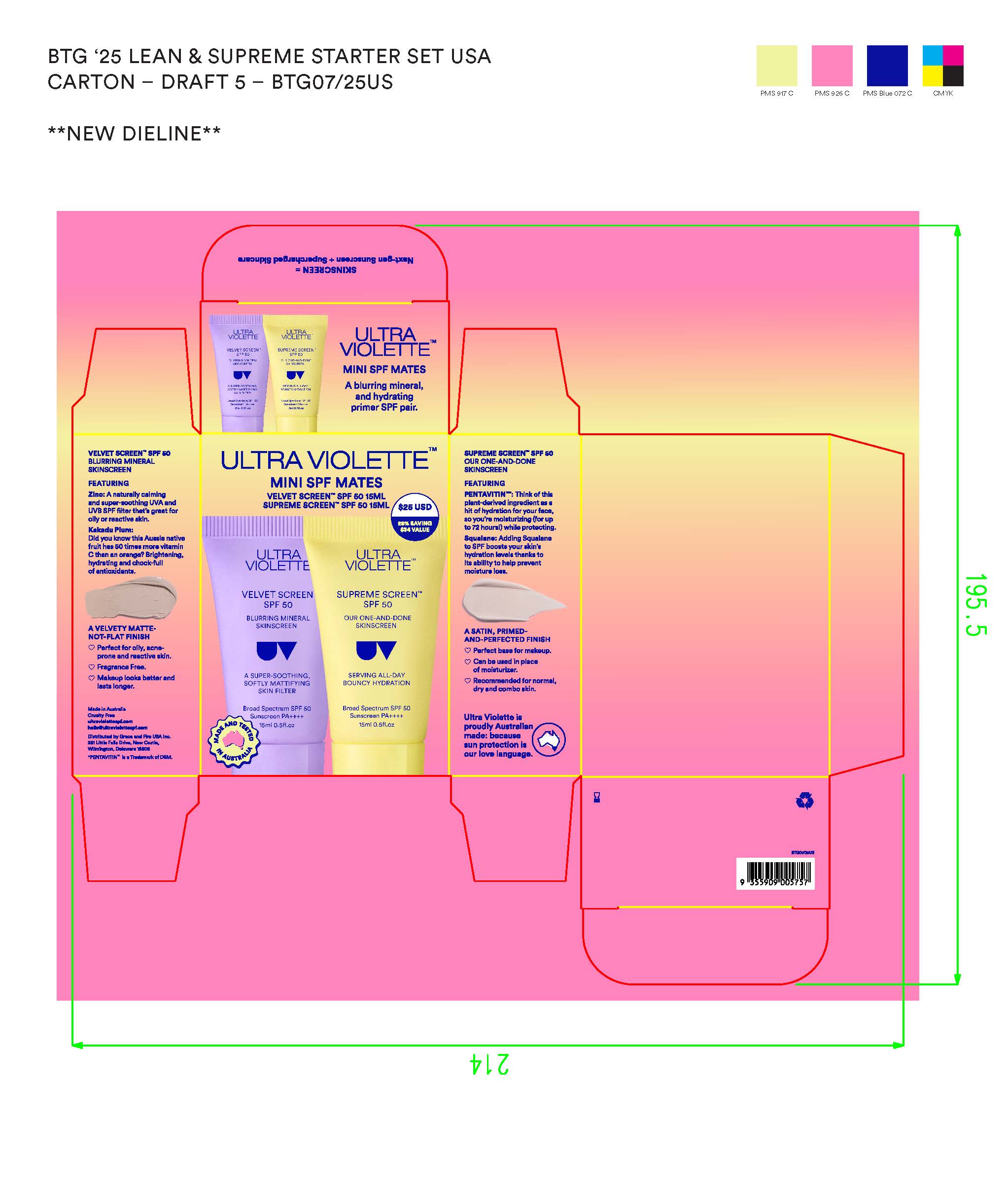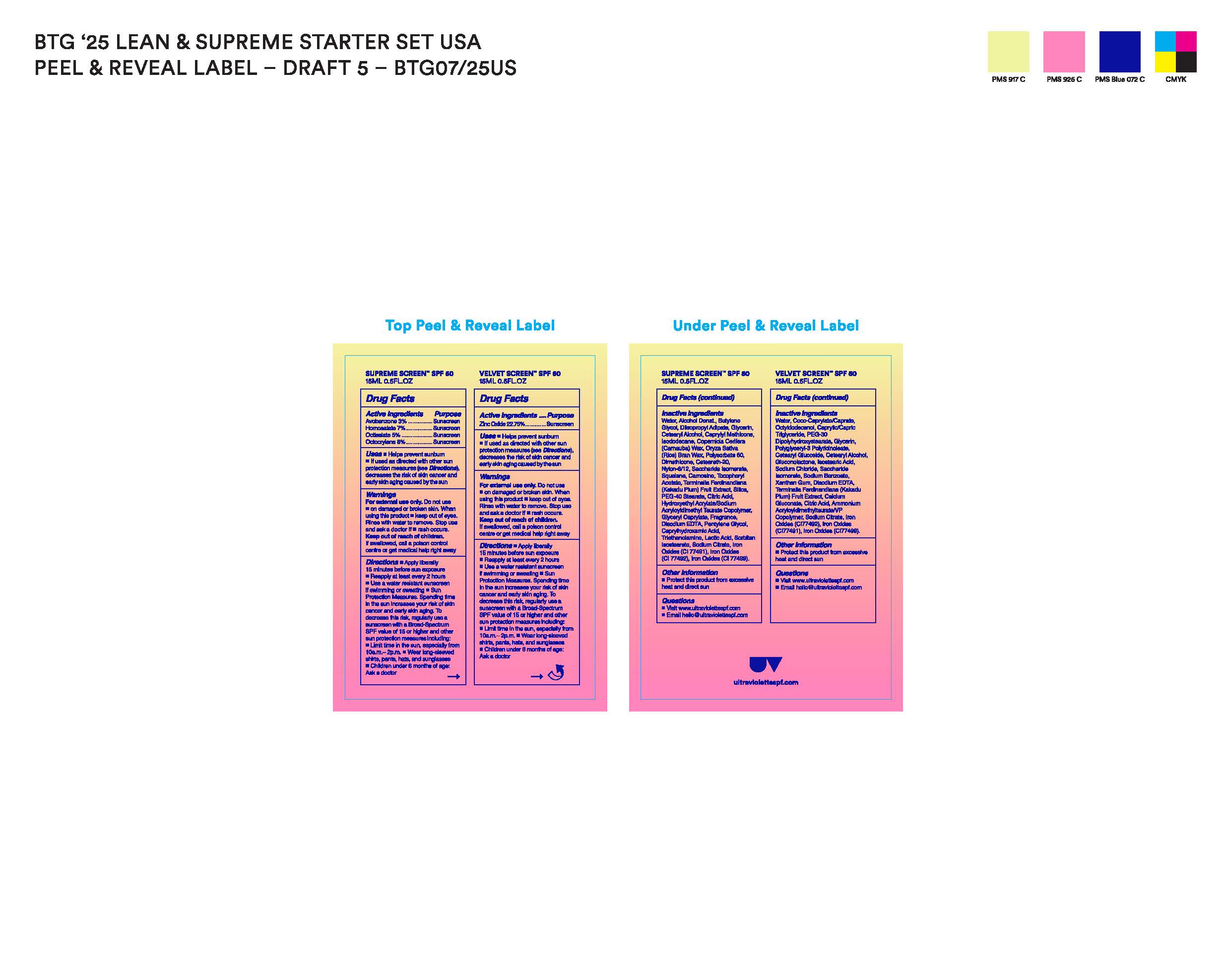 DRUG LABEL: Ultra Violette Mini Mates
NDC: 54394-110 | Form: KIT | Route: TOPICAL
Manufacturer: Thermo-Pak Company, Inc.
Category: otc | Type: HUMAN OTC DRUG LABEL
Date: 20241228

ACTIVE INGREDIENTS: ZINC OXIDE 22.75 g/100 mL; OCTOCRYLENE 8 g/100 mL; OCTISALATE 5 g/100 mL; HOMOSALATE 7 g/100 mL; AVOBENZONE 3 g/100 mL
INACTIVE INGREDIENTS: OCTYLDODECANOL; 2-ACETAMIDO-2-DEOXY-D-GLUCONO-1,5-LACTONE; AMMONIUM ACRYLOYLDIMETHYLTAURATE/VP COPOLYMER; POLYGLYCERYL-3 PENTARICINOLEATE; CITRIC ACID ACETATE; EDETATE DISODIUM; SACCHARIDE ISOMERATE; CETEARYL ALCOHOL; XANTHAN GUM; ISOSTEARIC ACID; CALCIUM GLUCONATE; PEG-30 DIPOLYHYDROXYSTEARATE; CETEARYL GLUCOSIDE; SODIUM CHLORIDE; GLYCERIN; CI 77499; CAPRYLIC/CAPRIC TRIGLYCERIDE; KAKADU PLUM; CI 77491; COCO-CAPRYLATE/CAPRATE; CI 77492; WATER; SODIUM CITRATE; SODIUM BENZOATE; TROLAMINE; FERRIC OXIDE RED; CAPRYLHYDROXAMIC ACID; LACTIC ACID; CARNAUBA WAX; DIMETHICONE; CAPRYLYL TRISILOXANE; CETOSTEARYL ALCOHOL; SQUALANE; CI 77492; SILICON DIOXIDE; GLYCERYL CAPRYLATE; SORBITAN ISOSTEARATE; FERROSOFERRIC OXIDE; BUTYLENE GLYCOL; GLYCERIN; POLYSORBATE 60; POLYOXYL 20 CETOSTEARYL ETHER; SACCHARIDE ISOMERATE; EDETATE DISODIUM; CARNOSINE; PEG-40 MONOSTEARATE; HYDROXYETHYL ACRYLATE/SODIUM ACRYLOYLDIMETHYL TAURATE COPOLYMER (100000 MPA.S AT 1.5%); SODIUM CITRATE; CITRIC ACID MONOHYDRATE; PENTYLENE GLYCOL; KAKADU PLUM; WATER; ALCOHOL; RICE BRAN; DIISOPROPYL ADIPATE; ISODODECANE; .ALPHA.-TOCOPHEROL ACETATE; NYLON-12

Ultra Violette Mini SPF Mates Duo Pack Contains
1 X Velvet Screen SPF50 15mL
1 X Supreme Screen SPF50 15mL

Active Ingredients

ACTIVE INGREDIENTS : VELVET SCREEN SPF 50

ZINC OXIDE 22.75%

ACTIVE INGRDIENTS : SUPREME SCREEN SPF 50

Avobenzone 3%

Homosalate 7%

Octisalate 5%

Octocrylene 8%

Purpose

Sunscreen

Uses

Uses  Helps prevent sunburn
 If used as directed with other sun
protection measures (see Directions),
decreases the risk of skin cancer and
early skin aging caused by the sun

Warnings

For External use Only

Do not use

- on damaged or broken skin, when using this product

- keep out of eyes rinse with water to remove

Stop use and ask doctor if

- rash occur

Keep out of reach of children

if swallowed , call a poison control centre or get medical help right away

Directions

 Apply liberally 15 minutes before
sun exposure  Reapply at least
every 2 hours  Use a water
resistant sunscreen if swimming
or sweating  Sun Protection
Measures. Spending time in the sun
increases your risk of skin cancer
and early skin aging. To decrease
this risk, regularly use a sunscreen
with a Broad-Spectrum SPF value of
15 or higher and other sun protection
measures including:  Limit time in
the sun, especially from 10a.m.–
2p.m.  Wear long-sleeved shirts,
pants, hats, and sunglasses
 Children under 6 months of age:
Ask a doctor

Inactive Ingredients

Inactive Ingredients : VELVET SCREEN SPF
Water, Coco-Caprylate/Caprate,
Octyldodecanol, Caprylic/Capric
Triglyceride, PEG-30
Dipolyhydroxystearate, Glycerin,
Polyglyceryl-3 Polyricinoleate,
Cetearyl Glucoside, Cetearyl Alcohol,
Gluconolactone, Isostearic Acid,
Sodium Chloride, Saccharide
Isomerate, Sodium Benzoate,
Xanthan Gum, Disodium EDTA,
Terminalia Ferdinandiana (Kakadu
Plum) Fruit Extract, Calcium
Gluconate, Citric Acid, Ammonium
Acryloyldimethyltaurate/VP
Copolymer, Sodium Citrate, Iron
Oxides (CI77492), Iron Oxides
(CI77491), Iron Oxides (CI77499).

Inactive Ingredients : SUPREME SCREEN SPF 50
Water, Alcohol Denat., Butylene Glycol, Diisopropyl Adipate, Glycerin, Cetearyl Alcohol, Caprylyl Methicone, Isododecane, Copernicia Cerifera (Camauba) Wax, Oryza Sativa (Rice) Bran Wax, Polysorbale 60, Dimethicone, Ceteareth-20, Nylon-6/12, Saccharide Isamerate, Squalane, Camosine, Tocopheryl Acetate, Terminalia Ferdinandiana (Kakadu Plum) Fruit Extract, Silica, PEG-40 Stearate, Citric Acid, Hydroxyelnyl Acrlale/Sodiumm
Acryloyloimelnyl Taurale Copolymer, Glyceryl Capryllate, Fragrance, Disodium EDTA, Pentylene Clyool, Caprylhydraxamio Acid,
Triethanolamino, Laotic Aoid, Sorbitan Isostearate, Sodium Citrate, Iron Oxides (C| 77491), Iron Oxides (C|77492), Iron Oxides (C| 77499).

Other Information

Protect this product from excessive heat and direct sun

Broad Spectrum SPF 50
Sunscreen PA++++
15ml